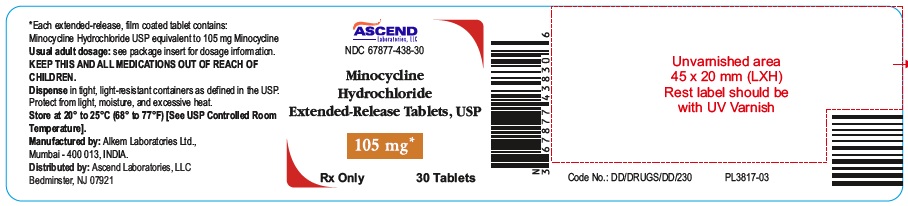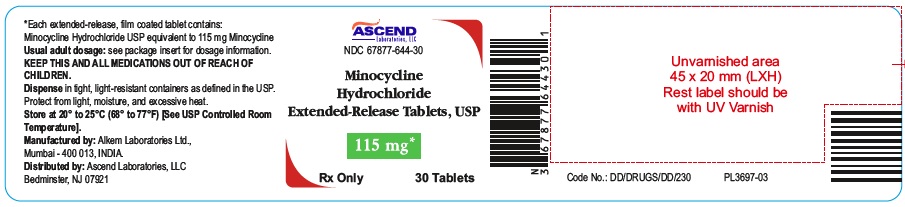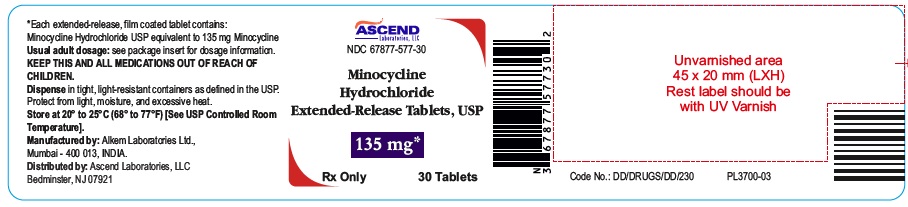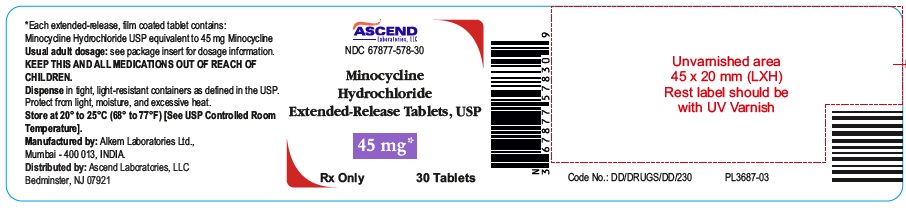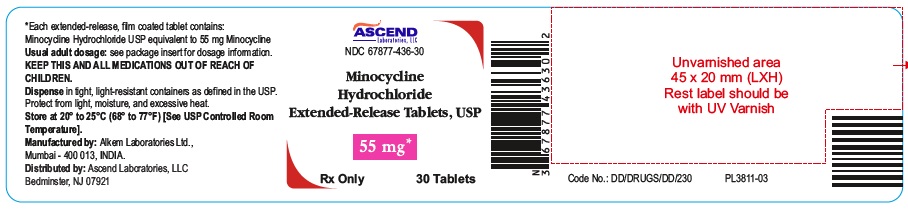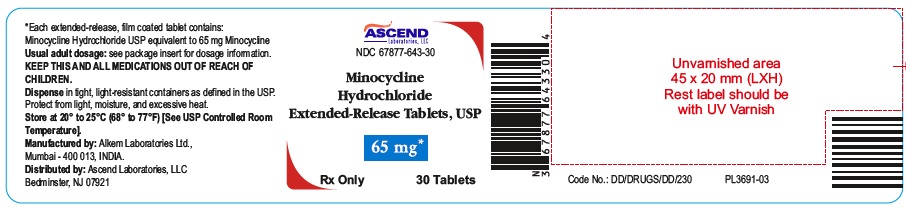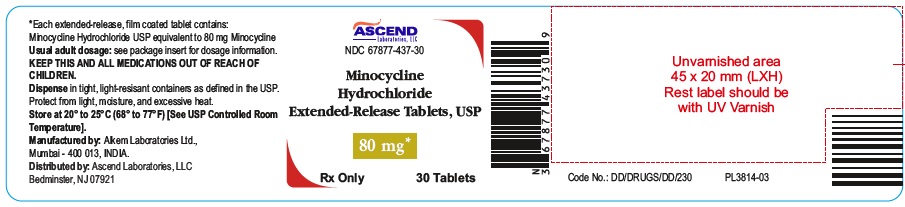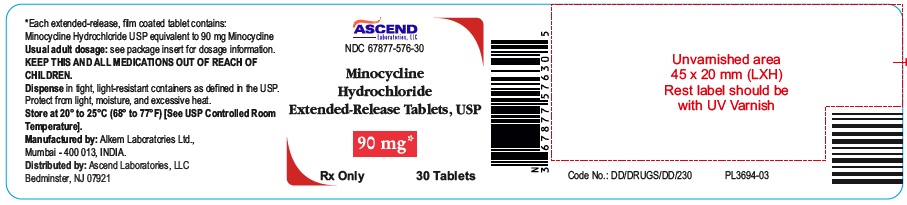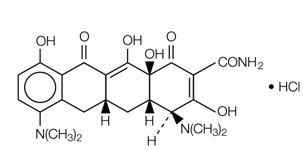 DRUG LABEL: Minocycline Hydrochloride
NDC: 67877-578 | Form: TABLET, FILM COATED, EXTENDED RELEASE
Manufacturer: Ascend Laboratories, LLC
Category: prescription | Type: Human Prescription Drug Label
Date: 20251218

ACTIVE INGREDIENTS: MINOCYCLINE HYDROCHLORIDE 45 mg/1 1
INACTIVE INGREDIENTS: LACTOSE MONOHYDRATE; HYPROMELLOSE 2208 (4000 MPA.S); HYPROMELLOSE 2910 (50 MPA.S); SILICON DIOXIDE; MAGNESIUM STEARATE; TITANIUM DIOXIDE; TRIACETIN; FERROSOFERRIC OXIDE

HIGHLIGHTS OF PRESCRIBING INFORMATION

These highlights do not include all the information needed to use MINOCYCLINE HYDROCHLORIDE EXTENDED-RELEASE TABLETS safely and effectively. See full prescribing information for MINOCYCLINE HYDROCHLORIDE EXTENDED-RELEASE TABLETS.
MINOCYCLINE HYDROCHLORIDE extended-release tablets, for oral use
Initial U.S. Approval: 1971

1 INDICATIONS & USAGE

Minocycline hydrochloride extended-release tablets is a tetracycline-class drug indicated to treat inflammatory lesions of non-nodular moderate to severe acne vulgaris in patients 12 years of age and older. (1)

Limitations of Use

This formulation of minocycline has not been evaluated in the treatment of infections. To reduce the development of drug-resistant bacteria and to maintain the effectiveness of other antibacterial drugs, use minocycline hydrochloride extended-release tablets only as indicated. (1)

2 DOSAGE & ADMINISTRATION

The recommended dosage of Minocycline hydrochloride extended-release tablets is approximately 1 mg/kg once daily for 12 weeks. (2)

3 DOSAGE FORMS & STRENGTHS

Extended-release tablets: 45 mg, 55 mg, 65 mg, 80 mg, 90 mg, 105 mg, 115 mg, and 135 mg (3)

4 CONTRAINDICATIONS

Known hypersensitivity to any of the tetracyclines. (4)

5 WARNINGS AND PRECAUTIONS

- Serious Skin/Hypersensitivity Reactions: Minocycline has been associated with anaphylaxis, serious skin reactions, erythema multiforme, and drug rash with eosinophilia and systemic symptoms (DRESS) syndrome. Discontinue immediately if symptoms occur. (5.1)
- Tooth Discoloration and Enamel Hypoplasia: Use during the second and third trimesters of pregnancy, infancy, and childhood up to the age of 8 years may cause permanent discoloration of the teeth (yellow-gray-brown). (5.2, 8.1, 8.4)
- Inhibition of Bone Growth: Use during the second and third trimesters of pregnancy, infancy, and childhood up to the age of 8 years may cause reversible inhibition of bone growth. (5.3, 8.1, 8.4)
- Clostridioides difficile-Associated Diarrhea (Antibiotic-Associated Colitis): Discontinue if Clostridioides difficile-associated diarrhea (antibiotic-associated colitis) occurs. (5.4)
- Hepatotoxicity: Discontinue if liver injury is suspected. (5.5)
- Central Nervous System Effects: May cause central nervous system side effects including light-headedness, dizziness, or vertigo. (5.6)
- Idiopathic Intracranial Hypertension: May cause idiopathic intracranial hypertension in adults and adolescents. Discontinue if symptoms occur. (5.7)
- Autoimmune Syndromes: Minocycline has been associated with autoimmune syndromes; discontinue immediately if symptoms occur. (5.8)
- Metabolic Effects: If renal impairment exists, reduce minocycline hydrochloride extended-release tablets dosage. (5.9)

6 ADVERSE REACTIONS

The most commonly observed adverse reactions (incidence ≥ 5%) are headache, fatigue, dizziness, and pruritus. (6.1)

To report SUSPECTED ADVERSE REACTIONS, contact Ascend Laboratories, LLC at 1-877-272-7901 or FDA at 1-800-FDA-1088 or www.fda.gov/medwatch.

7 DRUG INTERACTIONS

Patients who are on anticoagulant therapy may require downward adjustment of their anticoagulant dosage. (7.1)

8 USE IN SPECIFIC POPULATIONS

Lactation: Breastfeeding is not recommended. (8.2)

FULL PRESCRIBING INFORMATION

1 INDICATIONS & USAGE

Minocycline hydrochloride extended-release tablets is indicated to treat inflammatory lesions of non-nodular moderate to severe acne vulgaris in patients 12 years of age and older.

Limitations of Use

- Minocycline hydrochloride extended-release tablets did not demonstrate any effect on non-inflammatory acne lesions.
- This formulation of minocycline has not been evaluated in the treatment of infections [see Clinical Studies (14)].
- To reduce the development of drug-resistant bacteria as well as to maintain the effectiveness of other antibacterial drugs, use minocycline hydrochloride extended-release tablets only as indicated [see Warnings and Precautions (5.12)].

2 DOSAGE & ADMINISTRATION

The recommended dosage of minocycline hydrochloride extended-release tablets is approximately 1 mg/kg once daily for 12 weeks. Table 1 provides the recommended minocycline hydrochloride extended-release tablets dosage based upon weight ranges.

Table 1: Dosing Table for Minocycline hydrochloride extended-release tablets

Patient's Weight(kg) | Recommended Dosage (mg/day)
45 to 49 | 45
50 to 59 | 55
60 to 71 | 65
72 to 84 | 80
85 to 96 | 90
97 to 110 | 105
111 to 125 | 115
126 to 136 | 135

Higher dosages have not shown to be of additional benefit in the treatment of inflammatory lesions of acne and may be associated with more acute vestibular adverse reactions.

Swallow tablets whole. Do not chew, crush, or split the extended-release tablets.

Administer minocycline hydrochloride extended-release tablets with or without food [see Clinical Pharmacology (12.3)]. Ingestion of food along with minocycline hydrochloride extended-release tablets may help reduce the risk of esophageal irritation and ulceration.

In patients with renal impairment, decrease the daily dosage by either reducing the recommended individual doses and/or by extending the time intervals between doses [see Warnings and Precautions (5.9)].

3 DOSAGE FORMS & STRENGTHS

- 45 mg extended-release tablets: grey coloured capsule shaped film coated tablets, debossed with “45” on one side, plain on other side.
- 55 mg extended-release tablets: Pink coloured capsule shaped film coated tablets, debossed with "55" on one side, plain on other side.
- 65 mg extended-release tablets: blue coloured capsule shaped film coated tablets, debossed with “65” on one side, plain on other side.
- 80 mg extended-release tablets: Greyish brown coloured capsule shaped film coated tablets, debossed with "80'' on one side, plain on other side.
- 90 mg extended-release tablets: yellow coloured capsule shaped film coated tablets, debossed with “90” on one side, plain on other side.
- 105 mg extended-release tablets: Purple coloured capsule shaped film coated tablets, debossed with "105'' on one side, plain on other side.
- 115 mg extended-release tablets: green coloured capsule shaped film coated tablets, debossed with “115” on one side, plain on other side.
- 135 mg extended-release tablets: pink (orange-brown) coloured capsule shaped film coated tablets, debossed with “135” on one side, plain on other side

4 CONTRAINDICATIONS

Minocycline hydrochloride extended-release tablets is contraindicated in patients with history of a hypersensitivity reaction to any of the tetracyclines [see Warnings and Precautions (5.1)].

5 WARNINGS AND PRECAUTIONS

5.1 Serious Skin/Hypersensitivity Reactions

Cases of anaphylaxis, serious skin reactions (e.g., Stevens-Johnson syndrome), erythema multiforme, and drug rash with eosinophilia and systemic symptoms (DRESS) syndrome have been reported postmarketing with minocycline use in patients with acne. DRESS syndrome consists of cutaneous reaction (such as rash or exfoliative dermatitis), eosinophilia, and one or more of the following visceral complications such as: hepatitis, pneumonitis, nephritis, myocarditis, and pericarditis. Fever and lymphadenopathy may be present. In some cases, death has been reported. If this syndrome is recognized, minocycline hydrochloride extended-release tablets should be discontinued immediately.

Fixed drug eruptions have occurred with minocycline and other tetracyclines. Worsening severity upon subsequent administrations, including generalized bullous fixed drug eruption, has been observed with other tetracyclines [see ADVERSE REACTIONS (6.2)]. If severe skin/hypersensitivity reactions occur, discontinue minocycline hydrochloride extended-release tablets and institute appropriate therapy.

5.2 Tooth Discoloration and Enamel Hypoplasia

The use of tetracycline-class drugs, including minocycline hydrochloride extended-release tablets, during tooth development (second and third trimesters of pregnancy, infancy, and childhood up to the age of 8 years) may cause permanent discoloration of the teeth (yellow-graybrown). Permanent discoloration of the teeth is more common during long-term use of tetracycline-class drugs but has been observed following repeated short-term courses. Enamel hypoplasia has also been reported. Use of minocycline hydrochloride extended-release tablets is not recommended during tooth development.

Advise the patient of the potential risk to the fetus if minocycline hydrochloride extended-release tablets is used during the second or third trimester of pregnancy [see Use in Specific Populations (8.1, 8.4)].

5.3 Inhibition of Bone Growth

The use of tetracycline-class drugs, including minocycline hydrochloride extended-release tablets, during the second and third trimesters of pregnancy, infancy, and childhood up to the age of 8 years may cause reversible inhibition of bone growth. All tetracyclines, including minocycline hydrochloride extended-release tablets, form a stable calcium complex in any bone-forming tissue. A decrease in fibula growth rate has been observed in premature human infants given oral tetracycline in doses of 25 mg/kg every 6 hours. This reaction was shown to be reversible when the drug was discontinued.

Advise the patient of the potential risk to the fetus if minocycline hydrochloride extended-release tablets is used during the second or third trimester of pregnancy [see Use in Specific Populations (8.1, 8.4)].

5.4 Clostridioides difficile Associated Diarrhea (Antibiotic Associated Colitis)

Clostridioides difficile-associated diarrhea (CDAD) has been reported with nearly all antibacterial agents, including minocycline, and may range in severity from mild diarrhea to fatal colitis.

C. difficile produces toxins A and B which contribute to the development of CDAD. Hypertoxin-producing strains of C. difficile cause increased morbidity and mortality, as these infections can be refractory to antimicrobial therapy and may require colectomy. CDAD must be considered in all patients who present with diarrhea following antibiotic use. Careful medical history is necessary since CDAD has been reported to occur over two months after the administration of antibacterial agents.

If CDAD is suspected or confirmed, discontinue minocycline hydrochloride extended-release tablets.

5.5 Hepatotoxicity

Postmarketing cases of serious liver injury, including irreversible drug-induced hepatitis and fulminant hepatic failure (sometimes fatal), have been reported with minocycline use in the treatment of acne. Discontinue minocycline hydrochloride extended-release tablets if liver injury is suspected.

5.6 Central Nervous System Effects

Central nervous system side effects including light-headedness, dizziness, or vertigo have been reported with minocycline therapy. Caution patients who experience these symptoms about driving vehicles or using hazardous machinery while on minocycline hydrochloride extended-release tablets. These symptoms may disappear during therapy and usually rapidly disappear when minocycline hydrochloride extended-release tablets is discontinued.

5.7 Idiopathic Intracranial Hypertension

Idiopathic intracranial hypertension has been associated with the use of tetracycline-class drugs, including minocycline hydrochloride extended-release tablets. Clinical manifestations of idiopathic intracranial hypertension include headache, blurred vision, diplopia, and vision loss; papilledema can be found on fundoscopy. Women of childbearing age who are overweight or have a history of idiopathic intracranial hypertension are at a greater risk for developing idiopathic intracranial hypertension. Avoid concomitant use of isotretinoin and minocycline hydrochloride extended-release tablets because isotretinoin, a systemic retinoid, is also known to cause idiopathic intracranial hypertension.

Permanent visual loss may exist, even after the medication is discontinued. If visual disturbance occurs during treatment, prompt ophthalmologic evaluation is warranted. Because intracranial pressure can remain elevated for weeks after drug cessation, monitor patients until they stabilize.

5.8 Autoimmune Syndromes

Tetracyclines have been associated with the development of autoimmune syndromes. The long-term use of minocycline in the treatment of acne has been associated with drug-induced lupus-like syndrome, autoimmune hepatitis, and vasculitis. Sporadic cases of serum sickness have presented shortly after minocycline use. Symptoms may be manifested by fever, rash, arthralgia, and malaise. Evaluate symptomatic patients. If symptoms occur, immediately discontinue use of minocycline hydrochloride extended-release tablets.

5.9 Metabolic Effects

The anti-anabolic action of the tetracyclines, including minocycline hydrochloride extended-release tablets, may cause an increase in blood urea nitrogen (BUN). In patients with significantly impaired renal function, higher serum levels of tetracycline-class drugs may lead to azotemia, hyperphosphatemia, and acidosis. If renal impairment exists, lower the total doses of minocycline hydrochloride extended-release tablets, and if therapy is prolonged, monitor serum levels minocycline hydrochloride extended-release tablets.

5.10 Photosensitivity

Photosensitivity manifested by an exaggerated sunburn reaction has been observed in some individuals taking tetracyclines, including minocycline. Advise patients to minimize or avoid exposure to natural or artificial sunlight (e.g., tanning beds or UVA/B treatment) while using minocycline hydrochloride extended-release tablets. Instruct patients to use sunscreen products and wear protective apparel (e.g., hat) when exposure to sun cannot be avoided.

5.11 Tissue Hyperpigmentation

Tetracycline-class antibiotics are known to cause hyperpigmentation. Tetracycline therapy may induce hyperpigmentation in many organs, including nails, bone, skin, eyes, thyroid, visceral tissue, oral cavity (e.g., teeth, mucosa, alveolar bone), sclerae, and heart valves. Skin and oral pigmentation has been reported to occur independently of time or amount of drug administration, whereas other tissue pigmentation has been reported to occur upon prolonged administration. Skin pigmentation includes diffuse pigmentation as well as over sites of scars or injury.

5.12 Development of Drug-Resistant Bacteria

Bacterial resistance to tetracyclines may develop in patients using minocycline hydrochloride extended-release tablets. Because of the potential for drug-resistant bacteria to develop during the use of minocycline hydrochloride extended-release tablets, it should be used only as indicated.

5.13 Superinfection

Use of minocycline hydrochloride extended-release tablets may result in overgrowth of non-susceptible organisms, including fungi. If superinfection occurs, discontinue minocycline hydrochloride extended-release tablets and institute appropriate therapy.

5.14 Laboratory Monitoring

Perform periodic laboratory evaluations of organ systems, including hematopoietic, renal, and hepatic studies.

6 ADVERSE REACTIONS

The following clinically significant adverse reactions are described elsewhere in the labeling:

- Serious Skin/Hypersensitivity Reactions [see Warnings and Precautions (5.1)]
- Clostridioides difficile-Associated Diarrhea (Antibiotic-Associated Colitis) [see Warnings and Precautions (5.4)]
- Hepatotoxicity [see Warnings and Precautions (5.5)]
- Central Nervous System Effects [see Warnings and Precautions (5.6)]
- Idiopathic Intracranial Hypertension [see Warnings and Precautions (5.7)]

6.1 Clinical Trials Experience

Because clinical trials are conducted under widely varying conditions, adverse reaction rates observed in the clinical trials of a drug cannot be directly compared to rates in the clinical trials of another drug and may not reflect the rates observed in practice.

The following table summarizes selected adverse reactions reported in clinical trials at a rate of ≥1% for minocycline hydrochloride extended-release tablets and higher than placebo.

Table 2: Selected Treatment-Emergent Adverse Reactions in at Least 1% of Clinical Trial Subjects and Higher than Placebo

Adverse Reactions | Minocycline Hydrochloride Extended-Release Tablets (1 mg/kg) N = 674 (%) | PLACEBO N = 364 (%)
At least one treatment-emergent event | 379 (56) | 197 (54)
Fatigue | 62 (9) | 24 (7)
Dizziness | 59 (9) | 17 (5)
Pruritus | 31 (5) | 16 (4)
Malaise | 26 (4) | 9 (3)
Somnolence | 13 (2) | 3 (1)
Urticaria | 10 (2) | 1 (0)
Tinnitus | 10 (2) | 5 (1)
Arthralgia | 9 (1) | 2 (0)
Vertigo | 8 (1) | 3 (1)

6.2 Postmarketing Experience

The following adverse reactions have been reported with minocycline hydrochloride use in a variety of indications. Because these reactions are reported voluntarily from a population of uncertain size, it is not always possible to reliably estimate their frequency or establish a causal relationship to drug exposure.

Skin and hypersensitivity reactions: anaphylaxis, angioedema, DRESS syndrome, erythema multiforme, Stevens- Johnson syndrome, acute febrile neutrophilic dermatosis (Sweet’s syndrome), fixed drug eruptions, balanitis, anaphylactoid purpura, photosensitivity, pigmentation of skin and mucous membranes.

Autoimmune conditions: polyarthralgia, pericarditis, exacerbation of systemic lupus, pulmonary infiltrates with eosinophilia, lupus-like syndrome.

Central nervous system: idiopathic intracranial hypertension, bulging fontanels in infants, decreased hearing.

Endocrine: brown-black microscopic thyroid discoloration, abnormal thyroid function.

Oncology: thyroid cancer.

Oral: glossitis, dysphagia, tooth discoloration.

Gastrointestinal: enterocolitis, pancreatitis, hepatitis, liver failure.

Renal: acute renal failure.

Hematology: hemolytic anemia, thrombocytopenia, eosinophilia.

7 DRUG INTERACTIONS

7.1 Anticoagulants

Because tetracyclines have been shown to depress plasma prothrombin activity, patients who are on anticoagulant therapy may require downward adjustment of their anticoagulant dosage.

7.2 Penicillin

Because bacteriostatic drugs may interfere with the bactericidal action of penicillin, avoid giving minocycline hydrochloride extended-release tablets in conjunction with penicillin.

7.3 Antacids and Iron Preparations

Absorption of tetracyclines is impaired by antacids containing aluminum, calcium, or magnesium and iron-containing preparations.

7.4 Drug/Laboratory Test Interactions

False elevations of urinary catecholamine levels may occur due to interference with the fluorescence test.

8 USE IN SPECIFIC POPULATIONS

8.1 Pregnancy

Risk Summary

Tetracycline class drugs, including minocycline hydrochloride extended-release tablets may cause permanent discoloration of deciduous teeth and reversible inhibition of bone growth when administered during the second and third trimesters of pregnancy [see Warnings and Precautions (5.2, 5.3) and Use in Specific Populations (8.4)]. A few postmarketing cases of limb reductions have been reported over decades of use; however, the association is unclear. The limited data from postmarketing reports are not sufficient to inform a drug-associated risk for birth defects or miscarriage.

In animal reproduction studies conducted in pregnant rats and rabbits, fetuses with bent limb bones were observed following oral administration of minocycline during organogenesis at systemic exposures 3 and 2 times, respectively, the exposure associated with the maximum recommended human dose (MRHD) (see Data).

If a patient becomes pregnant while taking this drug, advise the patient of the risk to the fetus and to discontinue treatment.

The background risk of major birth defects and miscarriage for the indicated population is unknown. All pregnancies have a background risk of birth defect, loss, or other adverse outcomes. In the U.S. general population, the estimated background risk of major birth defects and miscarriage in clinically recognized pregnancies is 2 to 4% and 15 to 20%, respectively.

Data

Human Data

The use of tetracycline class drugs, including minocycline hydrochloride extended-release tablets, during tooth development (second and third trimesters of pregnancy, infancy, and childhood up to the age of 8 years) may cause permanent discoloration of deciduous teeth (yellow-gray-brown). Permanent discoloration of the teeth is more common during long-term use of the drug but has been observed following repeated short-term courses [see Warnings and Precautions (5.2)].

Animal Data

Results of animal studies indicate that tetracyclines cross the placenta, are found in fetal tissues, and can cause delayed skeletal development in the developing fetus. Evidence of embryotoxicity has been noted in animals treated early in pregnancy [see Warnings and Precautions (5.3)].

Minocycline induced skeletal malformations (bent limb bones) in fetuses when administered to pregnant rats and rabbits during the period of organogenesis at doses of 30 mg/kg/day and 100 mg/kg/day, respectively (3 times the MRHD and 2 times the MRHD on an AUC comparison basis, respectively). Reduced mean fetal body weight was observed in studies in which minocycline was administered to pregnant rats at an oral dose of 10 mg/kg/day (approximately equal to the MRHD on an AUC comparison basis).

Minocycline was assessed for effects on peri- and post-natal development of rats in a study that involved oral administration to pregnant rats during the period of organogenesis through lactation at dosages of 5, 10, or 50 mg/kg/day. In this study, body weight gain was significantly reduced in pregnant females that received 50 mg/kg/day (2.5 times the MRHD on an AUC comparison basis). No effects of treatment on the duration of the gestation period or the number of live pups born per litter were observed. Gross external anomalies observed in offspring of animals that received minocycline included reduced body size, improperly rotated forelimbs, and reduced size of extremities. No effects were observed on the physical development, behavior, learning ability, or reproduction of the offspring of animals that received minocycline.

8.2 Lactation

Risk Summary

Tetracycline-class antibiotics, including minocycline, are present in breast milk following oral administration. There are no data on the effects of minocycline on milk production. Because of the potential for serious adverse reactions, including tooth discoloration and inhibition of bone growth, advise patients that breastfeeding is not recommended during minocycline hydrochloride extended-release tablets therapy and for 4 days after the final dose [see Warnings and Precautions (5.2, 5.3)].

8.4 Pediatric Use

The safety and effectiveness of minocycline hydrochloride extended-release tablets have been established in pediatric patients 12 years of age and older for the treatment of inflammatory lesions of non-nodular moderate to severe acne vulgaris [see Clinical Studies (14)]. Tooth discoloration and inhibition of bone growth have been observed in pediatric patients [see Warnings and Precaution (5.2, 5.3)]. Use of tetracycline-class antibiotics below the age of 8 is not recommended due to the potential for tooth discoloration [see Warnings and Precautions (5.2)].

Safety and effectiveness of minocycline hydrochloride extended-release tablets have not been established in pediatric patients younger than 12 years of age.

8.5 Geriatric Use

Clinical studies of minocycline hydrochloride extended-release tablets did not include sufficient numbers of subjects aged 65 and over to determine whether they respond differently from younger subjects. Other reported clinical experience has not identified differences in responses between the elderly and younger patients. In general, dose selection for an elderly patient should be cautious, usually starting at the low end of the dosing range, reflecting the greater frequency of decreased hepatic, renal, or cardiac function, and concomitant disease or other drug therapy.

10 OVERDOSAGE

Minocycline is not removed in significant quantities by hemodialysis or peritoneal dialysis. In case of overdosage, discontinue minocycline hydrochloride extended-release tablets, treat symptomatically, and institute supportive measures. Call Poison Control Center at 1-800-222-1222 for the latest recommendations.

11 DESCRIPTION

Minocycline hydrochloride, a semi synthetic derivative of tetracycline, is [4S-(4α,4aα,5aα, 12aα)]-4,7–Bis(dimethylamino)-1,4,4a,5,5a,6,11,12a-octahydro-3,10,12,12a-tetrahydroxy-1,11-dioxo-2-naphthacenecarboxamide monohydrochloride.

The structural formula is represented below:

C23H27N3O7•HCl M. W. 493.95

Minocycline hydrochloride extended-release tablets, USP for oral administration contain minocycline hydrochloride USP equivalent to 45 mg, 55 mg, 65 mg, 80 mg, 90 mg, 105 mg, 115 mg, and 135 mg of minocycline. In addition, 45 mg, 55 mg, 65 mg, 80 mg, 90 mg, 105 mg, 115 mg, and 135 mg tablets contain the following inactive ingredients: lactose monohydrate, hypromellose type 2910, hypromellose type 2208, colloidal silicon dioxide, magnesium stearate, titanium dioxide and triacetin.

The 45 mg tablets also contain iron oxide black.

The 65 mg tablets also contain FD&C blue #1/brilliant blue FCF aluminium lake,

polyethylene glycol 3350, FD&C blue #2/indigo carmine aluminum lake and D&C yellow #10 aluminum lake.

The 55 mg tablets also contain macrogol, FD&C RED #40.

The 80 mg tablets also contain macrogol, FD&C blue #2, FD&C red #40, FD&C yellow #6.

The 90 mg tablets also contain iron oxide yellow and polyethylene glycol 3350.

The 105 mg tablets also D&C red #27, macrogol, FD&C blue #1.

The 115 mg tablets also contain D&C yellow #10 aluminum lake, FD&C blue #1/brilliant blue FCF aluminium lake and FD&C blue #2/indigo carmine aluminum lake.

The 135 mg tablets also contain polyethylene glycol 3350 and iron oxide red.

The USP Dissolution Test is pending.

12 CLINICAL PHARMACOLOGY

12.1 Mechanism of Action

The mechanism of action of minocycline hydrochloride extended-release tablets for the treatment of acne is unknown.

12.2 Pharmacodynamics

The pharmacodynamics of minocycline hydrochloride extended-release tablets for the treatment of acne are unknown.

12.3 Pharmacokinetics

Minocycline hydrochloride extended-release tablets are not bioequivalent to non-modified release minocycline products. Based on pharmacokinetic studies in healthy adults, minocycline hydrochloride extended-release tablets produce a delayed Tmax at 3.5 to 4.0 hours as compared to a non-modified release reference minocycline product (Tmax at 2.25 to 3 hours). At steady-state (Day 6), the mean AUC (0–24) and Cmax were 33.32 mcg×hr/mL and 2.63 mcg/mL for minocycline hydrochloride extended-release tablets and 46.35 mcg×hr/mL and 2.92 mcg/mL for minocycline hydrochloride capsules, respectively. These parameters are based on dose adjusted to 135 mg/day for both products.

A single-dose, four-way crossover study demonstrated that minocycline hydrochloride extended-release tablets used in the study (45 mg, 90 mg, 135 mg) exhibited dose-proportional pharmacokinetics. In another single-dose, five-way crossover pharmacokinetic study, minocycline hydrochloride extended-release tablets 55 mg, 80 mg, and 105 mg were shown to be doseproportional to minocycline hydrochloride extended-release tablets 90 mg and 135 mg.

When minocycline hydrochloride extended-release tablets were administered concomitantly with a meal that included dairy products, the extent and timing of absorption of minocycline did not differ from that of administration under fasting conditions.

Minocycline is lipid soluble and distributes into the skin and sebum.

13 NONCLINICAL TOXICOLOGY

13.1 Carcinogenesis & Mutagenesis & Impairment Of Fertility

In a carcinogenicity study in which minocycline HCl was orally administered to male and female rats once daily for up to 104 weeks at dosages up to 200 mg/kg/day, minocycline HCl was associated in both sexes with follicular cell tumors of the thyroid gland, including increased incidences of adenomas, carcinomas and the combined incidence of adenomas and carcinomas in males, and adenomas and the combined incidence of adenomas and carcinomas in females. In a carcinogenicity study in which minocycline HCl was orally administered to male and female mice once daily for up to 104 weeks at dosages up to 150 mg/kg/day, exposure to minocycline HCl did not result in a significantly increased incidence of neoplasms in either males or females.

Minocycline was not mutagenic in vitro in a bacterial reverse mutation assay (Ames test) or CHO/HGPRT mammalian cell assay in the presence or absence of metabolic activation. Minocycline was not clastogenic in vitro using human peripheral blood lymphocytes or in vivo in a mouse micronucleus test.

Male and female reproductive performance in rats was unaffected by oral doses of minocycline of up to 300 mg/kg/day (40 times the MRHD on an AUC comparison basis). However, oral administration of 100 or 300 mg/kg/day of minocycline to male rats (15 to 40 times the MRHD on an AUC comparison basis) adversely affected spermatogenesis. Effects observed at 300 mg/kg/day included a reduced number of sperm cells per gram of epididymis, an apparent reduction in the percentage of sperm that were motile, and (at 100 and 300 mg/kg/day) increased numbers of morphologically abnormal sperm cells. Morphological abnormalities observed in sperm samples included absent heads, misshapen heads, and abnormal flagella.

14 CLINICAL STUDIES

The safety and efficacy of minocycline hydrochloride extended-release tablets in the treatment of inflammatory lesions of non-nodular moderate to severe acne vulgaris was assessed in two 12-week, multi-center, randomized, double-blind, placebo-controlled trials in adult and pediatric subjects 12 years of age and older (Trial 1 and Trial 2). A total of 924 subjects with non-nodular moderate to severe acne vulgaris received minocycline hydrochloride extended-release tablets or placebo for a total of 12 weeks. The mean age of subjects was 20 years and subjects were from the following racial groups: White (73%), Hispanic (13%), Black (11%), Asian/Pacific Islander (2%), and Other (2%).

The two primary efficacy endpoints were:

1) Mean percent change in inflammatory lesion counts from Baseline to 12 weeks.

2) Percentage of subjects with an Evaluator's Global Severity Assessment (EGSA) of clear or almost clear at 12 weeks.

Efficacy results are presented in Table 4.

Table 4: Efficacy Results at Week 12 in Subjects with Non-nodular Moderate to Severe Acne Vulgaris in Trial 1 and Trial 2

 | Trial 1 |  |  | Trial 2
 | Minocycline hydrochloride extended-release tablets (1 mg/kg) N = 300 | Placebo N = 151 | Minocycline hydrochloride extended-release tablets (1 mg/kg) N = 315 |  | Placebo N = 158
Mean Percent Improvement in Inflammatory Lesions | 43.1% | 31.7% | 45.8% |  | 30.8%
No. (%) of Subjects Clear or Almost Clear on the EGSA* | 52 (17.3%) | 12 (7.9%) | 50 (15.9%) |  | 15 (9.5%)

*Evaluator's Global Severity Assessment

Minocycline hydrochloride extended-release tablets did not demonstrate any effect on non-inflammatory lesions (benefit or worsening).

16 HOW SUPPLIED/STORAGE AND HANDLING

How Supplied

Minocycline hydrochloride extended-release tablets, USP are supplied as aqueous film coated tablets containing Minocycline hydrochloride equivalent to 45 mg, 55 mg, 65 mg, 80 mg, 90 mg, 105 mg, 115 mg or 135 mg minocycline, are supplied as follows.

The 45 mg extended-release tablets are grey coloured capsule shaped film coated tablets, debossed with “45” on one side, plain on other side. Each tablet contains Minocycline hydrochloride equivalent to 45 mg minocycline, supplied as follows:

NDC 67877-578-14 | Carton of 140 (10 x 14 unit-dose)
NDC 67877-578-30 | Bottle of 30
NDC 67877-578-01 | Bottle of 100
NDC 67877-578-05 | Bottle of 500

The 55 mg extended-release tablets are Pink colored capsule shaped film coated tablets, debossed with "55" on one side, plain on other side. Each tablet contains Minocycline hydrochloride equivalent to 55 mg minocycline, supplied as follows:

NDC 67877-436-14 | Carton of 140 (10 x 14 unit-dose)
NDC 67877-436-30 | Bottle of 30
NDC 67877-436-01 | Bottle of 100
NDC 67877-436-05 | Bottle of 500

The 65 mg extended-release tablets are blue coloured capsule shaped film coated tablets, debossed with “65” on one side, plain on other side. Each tablet contains Minocycline hydrochloride equivalent to 65 mg minocycline, supplied as follows:

NDC 67877-643-14 | Carton of 140 (10 x 14 unit-dose)
NDC 67877-643-30 | Bottle of 30
NDC 67877-643-01 | Bottle of 100
NDC 67877-643-05 | Bottle of 500

The 80 mg extended-release tablets are Greyish brown colored capsule shaped film coated tablets, debossed with "80'' on one side, plain on other side. Each tablet contains Minocycline hydrochloride equivalent to 80 mg minocycline, supplied as follows:

NDC 67877-437-14 | Carton of 140 (10 x 14 unit-dose)
NDC 67877-437-30 | Bottle of 30
NDC 67877-437-01 | Bottle of 100
NDC 67877-437-05 | Bottle of 500

The 90 mg extended-release tablets are yellow coloured capsule shaped film coated tablets, debossed with “90” on one side, plain on other side. Each tablet contains Minocycline hydrochloride equivalent to 90 mg minocycline, supplied as follows:

NDC 67877-576-14 | Carton of 140 (10 x 14 unit-dose)
NDC 67877-576-30 | Bottle of 30
NDC 67877-576-01 | Bottle of 100
NDC 67877-576-05 | Bottle of 500

The 105 mg extended-release tablets are Purple colored capsule shaped film coated tablets, debossed with "105'' on one side, plain on other side. Each tablet contains Minocycline hydrochloride equivalent to 105 mg minocycline, supplied as follows:

NDC 67877-438-14 | Carton of 140 (10 x 14 unit-dose)
NDC 67877-438-30 | Bottle of 30
NDC 67877-438-01 | Bottle of 100
NDC 67877-438-05 | Bottle of 500

The 115 mg extended-release tablets are green coloured capsule shaped film coated tablets, debossed with “115” on one side, plain on other side. Each tablet contains Minocycline hydrochloride equivalent to 115 mg minocycline, supplied as follows:

NDC 67877-644-14 | Carton of 140 (10 x 14 unit-dose)
NDC 67877-644-30 | Bottle of 30
NDC 67877-644-01 | Bottle of 100
NDC 67877-644-05 | Bottle of 500

The 135 mg extended-release tablets are pink (orange brown) coloured capsule shaped film coated tablets, debossed with “135” on one side, plain on other side. Each tablet contains Minocycline hydrochloride equivalent to 135 mg minocycline, supplied as follows:

NDC 67877-577-14 | Carton of 140 (10 x 14 unit-dose)
NDC 67877-577-30 | Bottle of 30
NDC 67877-577-01 | Bottle of 100
NDC 67877-577-05 | Bottle of 500

Storage

Store at 20˚ to 25˚C (68˚ to 77˚ F) [See USP Controlled Room Temperature].

Handling

Keep out of reach of children.

Protect from light, moisture, and excessive heat.

Dispense in tight, light-resistant container with child-resistant closure.

17 PATIENT COUNSELING INFORMATION

Advise the patient to read the FDA-approved patient labeling (Patient Information).

Patients taking minocycline hydrochloride extended-release tablets should receive the following information and instructions:

Administration Instructions

- Minocycline hydrochloride extended-release tablets should be taken exactly as directed.

- Advise patients to swallow minocycline hydrochloride extended-release tablets whole and not to chew, crush, or split the tablets [see Dosage and Administration (2)].

Serious Skin/Hypersensitivity Reactions

- Inform patients that serious skin reactions have occurred with the minocycline use in patients with acne. Advise patients to discontinue use of minocycline hydrochloride extended-release tablets and contact their healthcare provider immediately at the first evidence of skin erythema [see Warnings and Precautions (5.1)].

Tooth Discoloration and Enamel Hypoplasia

- Advise patients that minocycline hydrochloride extended-release tablets use in pregnancy may cause permanent tooth discoloration of deciduous teeth. Advise patients to discontinue minocycline hydrochloride extended-release tablets during pregnancy and to inform their healthcare provider right away if they become pregnant during treatment [see Warnings and Precautions (5.2), Use in Specific Populations (8.1)].
- Advise caregivers of pediatric patients that minocycline hydrochloride extended-release tablets use may cause permanent discoloration of deciduous and permanent teeth [see Warnings and Precautions (5.2), Use in Specific Populations (8.4)].

Inhibition of Bone Growth

- Advise patients that minocycline hydrochloride extended-release tablets use in pregnancy may cause inhibition of fetal bone growth. Advise patients to discontinue minocycline hydrochloride extended-release tablets during pregnancy and to inform their healthcare provider right away if they become pregnant during treatment [see Warnings and Precautions (5.3), Use in Specific Populations (8.1)].

Clostridioides difficile-Associated Diarrhea (Antibiotic-Associated Colitis)

- Advise patients that Clostridioides difficile-associated diarrhea (antibiotic-associated colitis) can occur with minocycline therapy, including SOLODYN. If patients develop watery or bloody stools, advise patients to seek medical attention [see Warnings and Precautions (5.4)].

Hepatotoxicity

- Inform patients about the possibility of hepatotoxicity. Advise patients to seek medical advice if they experience signs or symptoms of hepatotoxicity, including loss of appetite, tiredness, diarrhea, jaundice, bleeding easily, confusion, and sleepiness [see Warnings and Precautions (5.5)].

Central Nervous System Effects

- Inform patients that central nervous system adverse reactions including dizziness or vertigo have been reported with oral minocycline therapy. Caution patients about driving vehicles or using hazardous machinery if they experience such symptoms while on minocycline hydrochloride extended-release tablets [see Warnings and Precautions (5.6)].

Idiopathic Intracranial Hypertension

- Inform patients that idiopathic intracranial hypertension can occur with minocycline therapy. Advise patients to seek medical attention if they develop unusual headache, visual symptoms, such as blurred vision, diplopia, and vision loss [see Warnings and Precautions (5.7)].

Autoimmune Syndromes

- Inform patients that autoimmune syndromes, including drug-induced lupus-like syndrome, autoimmune hepatitis, vasculitis, and serum sickness have been observed with tetracycline-class drugs, including minocycline. Symptoms may be manifested by arthralgia, fever, rash, and malaise. Advise patients who experience such symptoms to immediately discontinue minocycline hydrochloride extended-release tablets and seek medical help [see Warnings and Precautions (5.8)].

Photosensitivity

- Inform patients that photosensitivity manifested by an exaggerated sunburn reaction has been observed in some individuals taking tetracyclines, including minocycline. Advise patients to minimize or avoid exposure to natural or artificial sunlight (i.e., tanning beds or UVA/B treatment) while using minocycline hydrochloride extended-release tablets. Instruct patients to use sunscreen and wear protective clothing (e.g., hat) over treated areas when exposure to sun cannot be avoided [see Warnings and Precautions (5.10)].

Tissue Hyperpigmentation

- Inform patients that minocycline hydrochloride extended-release tablets may cause discoloration of skin, scars, teeth, or gums [see Warnings and Precautions (5.11)].

Lactation

- Advise patients that minocycline hydrochloride extended-release tablets therapy is not recommended during breast feeding for 4 days after the final dose [see Use in Specific Populations (8.2)].

Manufactured by:

Alkem Laboratories Ltd.,

Mumbai - 400 013, INDIA.

Distributed by:

Ascend Laboratories, LLC

Bedminster, NJ 07921

PATIENT INFORMATION

Minocycline hydrochloride

(min-oh-sye-kleen hye-droe-KLOR-ide)

extended-release tablets

What is minocycline hydrochloride extended-release tablets?

Minocycline hydrochloride extended-release tablets is a prescription medicine used to treat pimples and red bumps (non-nodular inflammatory lesions) that happen with moderate to severe acne vulgaris in people 12 years of age and older.

Minocycline hydrochloride extended-release tablets is not effective for acne that is not red-looking (non-inflammatory acne).

It is not known if minocycline hydrochloride extended-release tablets is:

- safe and effective for the treatment of infections.
- safe and effective in children under 12 years of age.

Who should not take minocycline hydrochloride extended-release tablets?

Do not take minocycline hydrochloride extended-release tablets if you are allergic to any tetracycline medicines. Ask your healthcare provider or pharmacist for a list of these medicines if you are not sure.

Before taking minocycline hydrochloride extended-release tablets, tell your healthcare provider about all of your medical conditions, including if you:

- have kidney problems
- have liver problems
- have diarrhea or watery stools
- have had increased pressure around your brain that may have caused vision problems
- are pregnant or plan to become pregnant. Minocycline hydrochloride extended-release tablets may harm your unborn baby. Taking minocycline hydrochloride extended-release tablets while you are pregnant may cause serious side effects on the growth of bone and teeth of your baby. Stop taking minocycline hydrochloride extended-release tablets and call your healthcare provider right away if you become pregnant during treatment with minocycline hydrochloride extended-release tablets.
- are breastfeeding or plan to breastfeed. Minocycline hydrochloride passes into your breast milk and may harm your baby. Do not breastfeed during treatment with minocycline hydrochloride extended-release tablets and for 4 days after your final dose.

Tell your healthcare provider about all the other medicines you take, including prescription and over-the-counter medicines, vitamins, and herbal supplements.

Minocycline hydrochloride extended-release tablets and other medicines may affect each other and can cause serious side effects. Minocycline hydrochloride extended-release tablets may affect the way other medicines work, and other medicines may affect how minocycline hydrochloride extended-release tablets works.

Especially tell your healthcare provider if you take:

- a blood thinner medicine
- a penicillin antibiotic medicine
- antacids that contain aluminum, calcium, or magnesium or iron-containing medicines
- an acne medicine that contains isotretinoin

Ask your healthcare provider or pharmacist if you are not sure if your medicine is one that is listed above.

Know the medicines you take. Keep a list of them to show your healthcare provider and pharmacist.

How should I take minocycline hydrochloride extended-release tablets?

- Take minocycline hydrochloride extended-release tablets exactly as your healthcare provider tells you.
- Take minocycline hydrochloride extended-release tablets 1 time per day with or without food. Taking minocycline hydrochloride extended-release tablets with food may lower your chances of getting irritation or ulcers in your esophagus. Your esophagus is the tube that connects your mouth to your stomach.
- Swallow minocycline hydrochloride extended-release tablets whole. Do not chew, crush, or split the tablets.

If you take too much minocycline hydrochloride extended-release tablets, stop taking minocycline hydrochloride extended-release tablets and call your healthcare provider or go to the nearest hospital emergency room, or contact a poison control center right away at 1-800-222-1222.

What should I avoid while taking minocycline hydrochloride extended-release tablets?

- You should not drive or operate dangerous machinery until you know how minocycline hydrochloride extended-release tablets affects you. Minocycline hydrochloride extended-release tablets may cause you to feel dizzy or light-headed or have a spinning feeling (vertigo).

- Avoid sunlight or artificial sunlight, such as sunlamps and tanning beds during treatment with minocycline hydrochloride extended-release tablets. Minocycline hydrochloride extended-release tablets can make your skin sensitive to the sun and artificial sunlight and you could get severe sunburn during treatment. Use sunscreen and wear a hat and protective clothing that covers your skin while out in the sunlight during treatment with minocycline hydrochloride extended-release tablets.

What are possible side effects of minocycline hydrochloride extended-release tablets?

Minocycline hydrochloride extended-release tablets may cause serious side effects, including:

- Serious skin and allergic reactions have happened during treatment with minocycline. Minocycline hydrochloride extended-release tablets may cause serious skin or allergic reactions that may also affect parts of your body such as your liver, lungs, kidneys, and heart. Sometimes these reactions can lead to death. Stop taking minocycline hydrochloride extended-release tablets and call your healthcare provider right away or go to the nearest hospital emergency room if you have any of the following signs or symptoms, including:
  - skin redness, rash, hives, sores in your mouth, or your skin blisters and peels
  - swelling of your face, eyes, lips, tongue, or throat
  - trouble swallowing or breathing
  - blood in your urine
  - fever, yellowing of the skin or the whites of your eyes (jaundice), dark colored urine
  - pain on the right side of the stomach area (abdominal pain)
  - chest pain or abnormal heartbeats
  - swelling in your legs, ankles, and feet
- Permanent tooth discoloration and problems with tooth enamel. Minocycline hydrochloride extended-release tablets may permanently turn a baby or child’s teeth yellow-gray-brown during tooth development. Minocycline hydrochloride extended-release tablets may also cause tooth enamel to not develop properly. You should not use minocycline hydrochloride extended-release tablets during tooth development. Tooth development happens in the second and third trimesters of pregnancy, and in children from birth to 8 years of age. See "What should I tell my healthcare provider before taking minocycline hydrochloride extended-release tablets?"
- Slow bone growth. Minocycline hydrochloride extended-release tablets may cause slow bone growth if it is used during the second and third trimesters of pregnancy and if it is used in infants and children up to 8 years of age. Slow bone growth is reversible after stopping treatment with minocycline hydrochloride extended-release tablets.
- Diarrhea (antibiotic associated colitis). Antibiotic associated colitis can happen with most antibiotics, including minocycline hydrochloride extended-release tablets. This type of diarrhea may be caused by an infection (Clostridioides difficile) in your intestines and can be severe and can lead to death. Call your healthcare provider right away if you get watery diarrhea, diarrhea that does not go away, or bloody stools.
- Liver problems. Minocycline hydrochloride extended-release tablets may cause serious liver problems that can lead to death. Stop taking minocycline hydrochloride extended-release tablets and call your healthcare provider right away if you get any of the following symptoms of liver problems:

- loss of appetite
- unexplained bleeding or bleeding more easily than normal
- tiredness
- diarrhea
- confusion
- yellowing of your skin or the whites of your eyes (jaundice)
- sleepiness

- Central nervous system effects. See "What should I avoid while taking minocycline hydrochloride extended-release tablets?" Central nervous system effects such as light-headedness, dizziness, and a spinning feeling (vertigo) may go away during your treatment with minocycline hydrochloride extended-release tablets or if treatment is stopped.
- Increased pressure around the brain (idiopathic intracranial hypertension). This condition may lead to vision changes and permanent vision loss. You are more likely to get intracranial hypertension if you are a female who can have children, are overweight, and have already had intracranial hypertension. Stop taking minocycline hydrochloride extended-release tablets and tell your healthcare provider right away if you have blurred vision, double vision, vision loss, or unusual headaches.
- Immune system reactions including a lupus-like syndrome, hepatitis, and inflammation of blood or lymph vessels (vasculitis). Using minocycline hydrochloride extended-release tablets for a long time to treat acne may cause immune system reactions. Stop taking minocycline hydrochloride extended-release tablets and tell your healthcare provider right away if you get a fever, rash, joint pain, or body weakness.
- Sensitivity to sunlight (photosensitivity). See “What should I avoid while taking SOLODYN?”
- Discoloration (tissue hyperpigmentation). Minocycline hydrochloride extended-release tablets may cause darkening of your nails, skin, eyes, teeth, gums, scars, and internal organs.

The most common side effects of minocycline hydrochloride extended-release tablets include:

- headache
- dizziness or spinning feeling
- tiredness
- itching

Your healthcare provider may do blood tests and check you for side effects during treatment with minocycline hydrochloride extended-release tablets and may lower your dose or stop treatment if you develop certain side effects.

These are not all of the possible side effects of minocycline hydrochloride extended-release tablets.

Call your doctor for medical advice about side effects. You may report side effects to FDA at 1-800-FDA-1088.

You may also report side effects to Bausch Health US, LLC at 1-800-321-4576.

How should I store minocycline hydrochloride extended-release tablets?

- Store minocycline hydrochloride extended-release tablets at room temperature between 68°F to 77°F (20°C to 25°C).
- Keep the minocycline hydrochloride extended-release tablets container tightly closed.
- Keep minocycline hydrochloride extended-release tablets away from light, moisture, and excessive heat.

Keep minocycline hydrochloride extended-release tablets and all medicines out of the reach of children.

General information about the safe and effective use of minocycline hydrochloride extended-release tablets.

Medicines are sometimes prescribed for purposes other than those listed in the Patient Information leaflet. Do not use minocycline hydrochloride extended-release tablets for a condition for which it was not prescribed. Do not give minocycline hydrochloride extended-release tablets to other people, even if they have the same symptoms you have. It may harm them. You can ask your pharmacist or healthcare provider for information about minocycline hydrochloride extended-release tablets that is written for health professionals.

What are the ingredients in minocycline hydrochloride extended-release tablets?

Active ingredient: minocycline hydrochloride

Inactive ingredients: lactose monohydrate, hypromellose type 2910, hypromellose type 2208, colloidal silicon dioxide, magnesium stearate, titanium dioxide and triacetin.

The 45 mg tablets also contain iron oxide black.

The 65 mg tablets also contain FD&C blue #1/brilliant blue FCF aluminium lake, polyethylene glycol 3350, FD&C blue #2/indigo carmine aluminum lake and D&C yellow #10 aluminum lake.

The 55 mg tablets also contain macrogol, FD&C RED #40.

The 80 mg tablets also contain macrogol, FD&C blue #2, FD&C red #40, FD&C yellow #6.

The 90 mg tablets also contain iron oxide yellow and polyethylene glycol 3350.

The 105 mg tablets also D&C red #27, macrogol, FD&C blue #1.

The 115 mg tablets also contain D&C yellow #10 aluminum lake, FD&C blue #1/brilliant blue FCF aluminium lake and FD&C blue #2/indigo carmine aluminum lake.

The 135 mg tablets also contain polyethylene glycol 3350 and iron oxide red.

Manufactured by:
Alkem Laboratories Ltd.,
Mumbai - 400 013, INDIA.
Distributed by:
Ascend Laboratories, LLC
Bedminster, NJ 07921

For more information, call 1-877-272-7901.

This Patient Information has been approved by the U.S. Food and Drug Administration.
Revised: October 2025
PT 3278-04

PACKAGE LABEL.PRINCIPAL DISPLAY PANEL

NDC 67877-578-30

Minocycline Hydrochloride Extended-Release Tablets, USP

45 mg

30 Tablets

NDC 67877-436-30

Minocycline Hydrochloride Extended-Release Tablets, USP

55 mg

30 Tablets

NDC 67877-643-30

Minocycline Hydrochloride Extended-Release Tablets, USP

65 mg

30 Tablets

NDC 67877-437-30

Minocycline Hydrochloride Extended-Release Tablets, USP

80 mg

30 Tablets

NDC 67877-576-30

Minocycline Hydrochloride Extended-Release Tablets, USP

90 mg

30 Tablets

NDC 67877-438-30

Minocycline Hydrochloride Extended-Release Tablets, USP

105 mg

30 Tablets

NDC 67877-644-30

Minocycline Hydrochloride Extended-Release Tablets, USP

115 mg

30 Tablets

NDC 67877-577-30

Minocycline Hydrochloride Extended-Release Tablets, USP

135 mg

30 Tablets